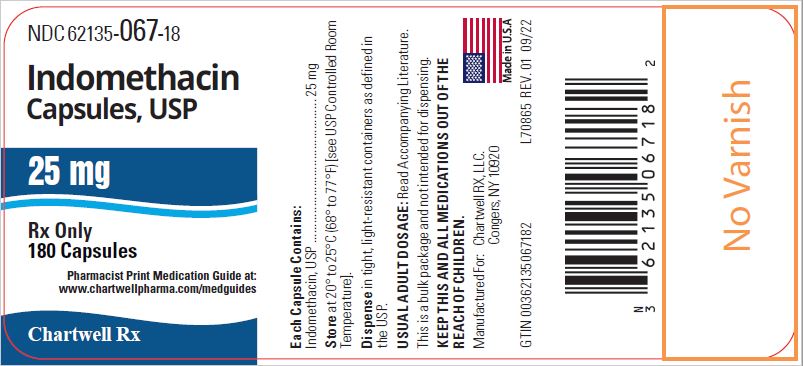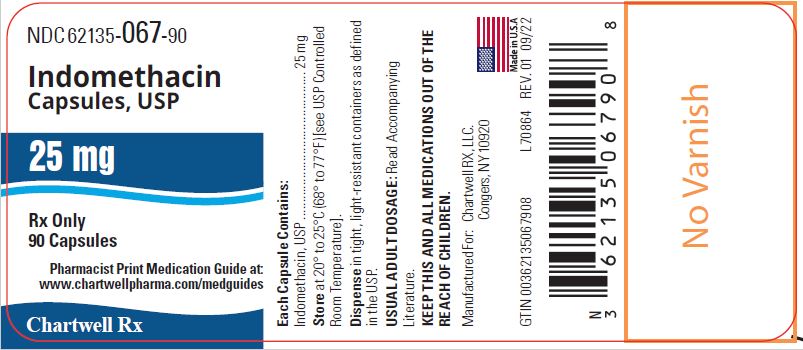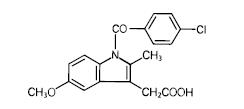 DRUG LABEL: INDOMETHACIN
NDC: 62135-067 | Form: CAPSULE
Manufacturer: Chartwell RX, LLC
Category: prescription | Type: HUMAN PRESCRIPTION DRUG LABEL
Date: 20250326

ACTIVE INGREDIENTS: INDOMETHACIN 25 mg/1 1
INACTIVE INGREDIENTS: STARCH, CORN; CROSCARMELLOSE SODIUM; LACTOSE MONOHYDRATE; POLYETHYLENE GLYCOL 4000; STEARIC ACID; TALC; D&C YELLOW NO. 10; FD&C GREEN NO. 3; GELATIN, UNSPECIFIED; TITANIUM DIOXIDE; ALCOHOL; FD&C BLUE NO. 1; FD&C BLUE NO. 2; FD&C RED NO. 40; FERROSOFERRIC OXIDE; BUTYL ALCOHOL; PROPYLENE GLYCOL; SHELLAC

Indomethacin Capsules, USP
25mg
Rx only

WARNING: RISK OF SERIOUS CARDIOVASCULAR AND GASTROINTESTINAL EVENTS

Cardiovascular Thrombotic Events

- Nonsteroidal anti-inflammatory drugs (NSAIDs) cause an increased risk of serious cardiovascular thrombotic events, including myocardial infarction and stroke, which can be fatal. This risk may occur early in treatment and may increase with duration of use (see WARNINGS).
- Indomethacin is contraindicated in the setting of coronary artery bypass graft (CABG) surgery (see CONTRAINDICATIONS and WARNINGS).

Gastrointestinal Risk

NSAIDs cause an increased risk of serious gastrointestinal adverse events including bleeding, ulceration, and perforation of the stomach or intestines, which can be fatal. These events can occur at any time during use and without warning symptoms. Elderly patients are at greater risk for serious gastrointestinal events. (See WARNINGS).

DESCRIPTION

Indomethacin capsules, USP for oral administration contains 25 mg of indomethacin. Each capsule contains the following inactive ingredients: corn starch, croscarmellose sodium, lactose monohydrate, polyethylene glycol 4000, stearic acid, and talc. The capsule shell contains D&C Yellow #10, FD&C Green #3, gelatin, and titanium dioxide. The black imprinting ink contains alcohol, black iron oxide, D&C Yellow #10, FD&C Blue #1, FD&C Blue #2, FD&C Red #40, ferrosoferric oxide, n-butyl alcohol, propylene glycol, and shellac glaze. Indomethacin is a nonsteroidal anti-inflammatory indole derivative designated chemically as 1 – (4-chlorobenzoyl)-5-methoxy-2-methyl-1 H-indole-3-acetic acid.

The structural formula is:

Indomethacin is practically insoluble in water and sparingly soluble in alcohol. It has a pKa of 4.5 and is stable in neutral or slightly acidic media and decomposes in strong alkali. The molecular weight of indomethacin is 357.79 and its molecular formula is C19H16C1NO4

CLINICAL PHARMACOLOGY

Indomethacin is a non-steroidal anti-inflammatory drug (NSAID) that exhibits antipyretic and analgesic properties. Its mode of action, like that of other anti-inflammatory drugs, is not known. However, its therapeutic action is not due to pituitary-adrenal stimulation.

Indomethacin is a potent inhibitor of prostaglandin synthesis in vitro. Concentrations are reached during therapy which have been demonstrated to have an effect in vivo as well. Prostaglandins sensitize afferent nerves and potentiate the action of bradykinin in inducing pain in animal models. Moreover, prostaglandins are known to be among the mediators of inflammation. Since indomethacin is an inhibitor of prostaglandin synthesis, its mode of action may be due to a decrease of prostaglandins in peripheral tissues.

Indomethacin has been shown to be an effective anti-inflammatory agent, appropriate for long-term use in rheumatoid arthritis, ankylosing spondylitis, and osteoarthritis.

Indomethacin affords relief of symptoms; it does not alter the progressive course of the underlying disease.

Indomethacin suppresses inflammation in rheumatoid arthritis as demonstrated by relief of pain, and reduction of fever, swelling and tenderness. Improvement in patients treated with indomethacin for rheumatoid arthritis has been demonstrated by a reduction in joint swelling, average number of joints involved, and morning stiffness; by increased mobility as demonstrated by a decrease in walking time; and by improved functional capability as demonstrated by an increase in grip strength. Indomethacin may enable the reduction of steroid dosage in patients receiving steroids for the more severe forms of rheumatoid arthritis. In such instances the steroid dosage should be reduced slowly and the patients followed very closely for any possible adverse effects.

Indomethacin has been reported to diminish basal and CO2 stimulated cerebral blood flow in healthy volunteers following acute oral and intravenous administration. In one study after one week of treatment with orally administered indomethacin, this effect on basal cerebral blood flow had disappeared. The clinical significance of this effect has not been established.

Indomethacin capsules have been found effective in relieving the pain, reducing the fever, swelling, redness, and tenderness of acute gouty arthritis — [see INDICATIONS AND USAGE] .

Following single oral doses of indomethacin capsules 25 mg or 50 mg, indomethacin is readily absorbed, attaining peak plasma concentrations of about 1 and 2 mcg/mL, respectively, at about 2 hours. Orally administered indomethacin capsules are virtually 100% bioavailable, with 90% of the dose absorbed within 4 hours. A single 50 mg dose of indomethacin oral suspension was found to be bioequivalent to a 50 mg indomethacin capsule when each was administered with food.

Indomethacin is eliminated via renal excretion, metabolism, and biliary excretion. Indomethacin undergoes appreciable enterohepatic circulation. The mean half-life of indomethacin is estimated to be about 4.5 hours. With a typical therapeutic regimen of 25 or 50 mg t.i.d., the steady-state plasma concentrations of indomethacin are an average 1.4 times those following the first dose.

Indomethacin exists in the plasma as the parent drug and its desmethyl, desbenzoyl, and desmethyl-desbenzoyl metabolites, all in the unconjugated form. About 60 percent of an oral dosage is recovered in urine as drug and metabolites (26 percent as indomethacin and its glucuronide), and 33 percent is recovered in feces (1.5 percent as indomethacin).

About 99% of indomethacin is bound to protein in plasma over the expected range of therapeutic plasma concentrations. Indomethacin has been found to cross the blood-brain barrier and the placenta.

INDICATIONS AND USAGE

Carefully consider the potential benefits and risks of indomethacin capsules, USP and other treatment options before deciding to use indomethacin. Use the lowest effective dose for the shortest duration consistent with individual patient treatment goals (see Warnings: Gastrointestinal Bleeding, Ulceration, and Perforation).

Indomethacin has been found effective in active stages of the following:

1. Moderate to severe rheumatoid arthritis including acute flares of chronic disease.

2. Moderate to severe ankylosing spondylitis.

3. Moderate to severe osteoarthritis.

4. Acute painful shoulder (bursitis and/or tendinitis).

5. Acute gouty arthritis.

CONTRAINDICATIONS

Indomethacin is contraindicated in patients with known hypersensitivity to indomethacin or the excipients (see Warnings; Anaphylactic/Anaphylactoid Reactions) .

Indomethacin should not be given to patients who have experienced asthma, urticaria, or allergic-type reactions after taking aspirin or other NSAIDs. Severe, rarely fatal, anaphylactic/anaphylactoid reactions to NSAIDs have been reported in such patients (see WARNINGS; Anaphylactic/Anaphylactoid Reactions, and PRECAUTIONS; Preexisting Asthma).

- Indomethacin is contraindicated in the setting of coronary artery bypass graft (CABG) surgery (see Warnings; Cardiovascular Thrombatic Events).

WARNINGS

Cardiovascular Thrombotic Events

Clinical trials of several COX-2 selective and nonselective NSAIDs of up to three years duration have shown an increased risk of serious cardiovascular (CV) thrombotic events, including myocardial infarction (MI) and stroke, which can be fatal. Based on available data, it is unclear that the risk for CV thrombotic events is similar for all NSAIDs. The relative increase in serious CV thrombotic events over baseline conferred by NSAID use appears to be similar in those with and without known CV disease or risk factors for CV disease. However, patients with known CV disease or risk factors had a higher absolute incidence of excess serious CV thrombotic events, due to their increased baseline rate. Some observational studies found that this increased risk of serious CV thrombotic events began as early as the first weeks of treatment. The increase in CV thrombotic risk has been observed most consistently at higher doses.

To minimize the potential risk for an adverse CV event in NSAID-treated patients, use the lowest effective dose for the shortest duration possible. Physicians and patients should remain alert for the development of such events, throughout the entire treatment course, even in the absence of previous CV symptoms. Patients should be informed about the symptoms of serious CV events and the steps to take if they occur.

There is no consistent evidence that concurrent use of aspirin mitigates the increased risk of serious CV thrombotic events associated with NSAID use. The concurrent use of aspirin and an NSAID, such as indomethacin, increases the risk of serious gastrointestinal (GI) events [see WARNINGS].

Status Post Coronary Artery Bypass Graft (CABG) Surgery

Two large, controlled clinical trials of a COX-2 selective NSAID for the treatment of pain in the first 10–14 days following CABG surgery found an increased incidence of myocardial infarction and stroke. NSAIDs are contraindicated in the setting of CABG [see CONTRAINDICATIONS ].

Post-MI Patients

Observational studies conducted in the Danish National Registry have demonstrated that patients treated with NSAIDs in the post-MI period were at increased risk of reinfarction, CV-related death, and all-cause mortality beginning in the first week of treatment. In this same cohort, the incidence of death in the first year post MI was 20 per 100 person years in NSAID-treated patients compared to 12 per 100 person years in non-NSAID exposed patients. Although the absolute rate of death declined somewhat after the first year post-MI, the increased relative risk of death in NSAID users persisted over at least the next four years of follow-up.

Avoid the use of indomethacin capsules in patients with a recent MI unless the benefits are expected to outweigh the risk of recurrent CV thrombotic events. If indomethacin capsules are used in patients with a recent MI, monitor patients for signs of cardiac ischemia.

Hypertension

NSAIDs, including indomethacin, can lead to onset of new hypertension or worsening of preexisting hypertension, either of which may contribute to the increased incidence of CV events. Patients taking thiazides or loop diuretics may have impaired response to these therapies when taking NSAIDs. NSAIDs, including indomethacin, should be used with caution in patients with hypertension. Blood pressure (BP) should be monitored closely during the initiation of NSAID treatment and throughout the course of therapy.

Heart Failure and Edema

The Coxib and traditional NSAID Trialists’ Collaboration meta-analysis of randomized controlled trials demonstrated an approximately two-fold increase in hospitalizations for heart failure in COX-2 selective-treated patients and nonselective NSAID-treated patients compared to placebo-treated patients. In a Danish National Registry study of patients with heart failure, NSAID use increased the risk of MI, hospitalization for heart failure, and death.

Additionally, fluid retention and edema have been observed in some patients treated with NSAIDs. Use of indomethacin may blunt the CV effects of several therapeutic agents used to treat these medical conditions [e.g., diuretics, ACE inhibitors, or angiotensin receptor blockers (ARBs)] [ see Precautions; Drug Interactions].

Avoid the use of indomethacin capsules in patients with severe heart failure unless the benefits are expected to outweigh the risk of worsening heart failure. If indomethacin capsules are used in patients with severe heart failure, monitor patients for signs of worsening heart failure.

Gastrointestinal Effects – Risk of Ulceration, Bleeding, and Perforation

NSAIDs, including indomethacin, can cause serious gastrointestinal (GI) adverse events including inflammation, bleeding, ulceration, and perforation of the esophagus, stomach, small intestine, or large intestine, which can be fatal. These serious adverse events can occur at any time, with or without warning symptoms, in patients treated with NSAIDs. Only one in five patients, who develop a serious upper GI adverse event on NSAID therapy is symptomatic. Upper GI ulcers, gross bleeding, or perforation caused by NSAIDs occur in approximately 1% of patients treated for 3-6 months, and in about 2-4% of patients treated for one year. These trends continue with longer duration of use, increasing the likelihood of developing a serious GI event at some time during the course of therapy. However, even short-term therapy is not without risk.

Rarely, in patients taking indomethacin, intestinal ulceration has been associated with stenosis and obstruction. Gastrointestinal bleeding without obvious ulcer formation and perforation of preexisting sigmoid lesions (diverticulum, carcinoma, etc.) has occurred. Increased abdominal pain in ulcerative colitis patients or the development of ulcerative colitis and regional ileitis have been reported to occur rarely.

NSAIDs should be prescribed with extreme caution in those with prior history of ulcer disease or gastrointestinal bleeding. Patients with a prior history of peptic ulcer disease and/or gastrointestinalbleeding who use NSAIDs have a greater than 10-fold increased risk for developing a GI bleed compared to patients without these risk factors. Other factors that increase the risk of GI bleeding in patients treated with NSAIDs include longer duration of NSAIDs therapy, concomitant use of oral corticosteroids, aspirin, anticoagulants, or selective serotonin reuptake inhibitors (SSRIs); smoking, use of alcohol, older age, and poor general health status. Most postmarketing reports of fatal GI events occured in elderly or debilitated patients. Additionally, patients with advanced liver disease and/or coagulopathy are at increased risk for GI bleeding.

To minimize the potential risk for an adverse GI event in patients treated with an NSAID, the lowest effective dose should be used for the shortest possible duration. Patients and physicians should remain alert for signs and symptoms of GI ulceration and bleeding during NSAID therapy and promptly initiate additional evaluation and treatment if a serious GI adverse event is suspected. This should include discontinuation of the NSAID until a serious GI adverse event is ruled out. For high risk patients, alternate therapies that do not involve NSAIDs should be considered.

Renal Effects

Long-term administration of NSAIDs has resulted in renal papillary necrosis and other renal injury.

Renal toxicity has also been seen in patients in whom renal prostaglandins have a compensatory role in the maintenance of renal perfusion. In these patients, administration of a nonsteroidal anti-inflammatory drug may cause a dose-dependent reduction in prostaglandin formation and, secondarily, in renal blood flow, which may precipitate over renal decompensation. Patients at greatest risk of this reaction are those with impaired renal function, heart failure, liver dysfunction, those taking diuretics and ACE inhibitors, patients with volume depletion, and the elderly. Discontinuation of NSAID therapy is usually followed by recovery to the pretreatment state.

It has been reported that the addition of the potassium-sparing diuretic, triamterene, to a maintenance schedule of indomethacin resulted in reversible acute renal failure in two of four healthy volunteers. Indomethacin and triamterene should not be administered together.

Increases in serum potassium concentration, including hyperkalemia, have been reported with use of indomethacin, even in some patients without renal impairment. In patients with normal renal function, these effects have been attributed to a hyporeninemic-hypoaldosteronism state [see PRECAUTIONS, Drug Interactions].

Indomethacin and potassium-sparing diuretics each may be associated with increased serum potassium levels. The potential effects of indomethacin and potassium-sparing diuretics on potassium kinetics and renal function should be considered when these agents are administered concurrently.

Advanced Renal Disease

No information is available from controlled clinical studies regarding the use of indomethacin in patients with advanced renal disease. Therefore, treatment with indomethacin is not recommended in these patients with advanced renal disease. If indomethacin therapy must be initiated, close monitoring of the patient’s renal function is advisable.

Anaphylactic/Anaphylactoid Reactions

As with other NSAIDs, anaphylactic/anaphylactoid reactions may occur in patients without known prior exposure to indomethacin. Indomethacin should not be given to patients with the aspirin triad. This symptom complex typically occurs in asthmatic patients who experience rhinitis with or without nasal polyps, or who exhibit severe, potentially fatal bronchospasm after taking aspirin or other NSAIDs [see CONTRAINDICATIONS and PRECAUTIONS –Preexisting Asthma]. Emergency help should be sought in cases where an anaphylactic/anaphylactoid reaction occurs.

Skin Reactions

NSAIDs, including indomethacin, can cause serious skin adverse events such as exfoliative dermatitis, Stevens - Johnson syndrome (SJS), and toxic epidermal necrolysis (TEN), which can be fatal. These serious events may occur without warning. Patients should be informed about the signs and symptoms of serious skin manifestations and use of the drug should be discontinued at the first appearance of skin rash or any other sign of hypersensitivity.

Drug Rash with Eosinophilia and Systemic Symptoms (DRESS)

Drug Reaction with Eosinophilia and Systemic Symptoms (DRESS) has been reported in patients taking NSAIDs such as indomethacin capsules. Some of these events have been fatal or life-threatening. DRESS typically, although not exclusively, presents with fever, rash, lymphadenopathy, and/or facial swelling.

Other clinical manifestations may include hepatitis, nephritis, hematological abnormalities, myocarditis, or myositis. Sometimes symptoms of DRESS may resemble an acute viral infection. Eosinophilia is often present. Because this disorder is variable in its presentation, other organ systems not noted here may be involved. It is important to note that early manifestations of hypersensitivity, such as fever or lymphadenopathy, may be present even though rash is not evident. If such signs or symptoms are present, discontinue indomethacin capsules and evaluate the patient immediately.

Fetal Toxicity

Premature Closure of Fetal Ductus Arteriosus:

Avoid use of NSAIDs, including indomethacin capsules, in pregnant women at about 30 weeks gestation and later. NSAIDs including indomethacin capsules, increase the risk of premature closure of the fetal ductus arteriosus at approximately this gestational age.

Oligohydramnios/Neonatal Renal Impairment:

Use of NSAIDs, including indomethacin capsules, at about 20 weeks gestation or later in pregnancy may cause fetal renal dysfunction leading to oligohydramnios and, in some cases, neonatal renal impairment. These adverse outcomes are seen, on average, after days to weeks of treatment, although oligohydramnios has been infrequently reported as soon as 48 hours after NSAID initiation. Oligohydramnios is often, but not always, reversible with treatment discontinuation. Complications of prolonged oligohydramnios may, for example, include limb contractures and delayed lung maturation. In some postmarketing cases of impaired neonatal renal function, invasive procedures such as exchange transfusion or dialysis were required.

If NSAID treatment is necessary between about 20 weeks and 30 weeks gestation, limit indomethacin capsules use to the lowest effective dose and shortest duration possible. Consider ultrasound monitoring of amniotic fluid if indomethacin capsules treatment extends beyond 48 hours. Discontinue indomethacin capsules if oligohydramnios occurs and follow up according to clinical practice [ see PRECAUTIONS; Pregnancy].

Ocular Effects

Corneal deposits and retinal disturbances, including those of the macula, have been observed in some patients who had received prolonged therapy with indomethacin. The prescribing physician should be alert to the possible association between the changes noted and indomethacin. It is advisable to discontinue therapy if such changes are observed. Blurred vision may be a significant symptom and warrants a thorough ophthalmological examination. Since these changes may be asymptomatic, ophthalmologic examination at periodic intervals is desirable in patients where therapy is prolonged.

Central Nervous System Effects:

Indomethacin may aggravate depression or other psychiatric disturbances, epilepsy, and parkinsonism, and should be used with considerable caution in patients with these conditions. If severe CNS adverse reactions develop, indomethacin should be discontinued.

Indomethacin may cause drowsiness; therefore, patients should be cautioned about engaging in activities requiring mental alertness and motor coordination, such as driving a car. Indomethacin may also cause headache. Headache which persists despite dosage reduction requires cessation of therapy with indomethacin.

PRECAUTIONS

General

Indomethacin cannot be expected to substitute for corticosteroids or to treat corticosteroid insufficiency.

Abrupt discontinuation of corticosteroids may lead to disease exacerbation. Patients on prolonged corticosteroid therapy should have their therapy tapered slowly if a decision is made to discontinue corticosteroids.

The pharmacological activity of indomethacin in reducing fever and inflammation may diminish the utility of these diagnostic signs in detecting complications of presumed noninfectious, painful conditions.

Hepatic Effects

Borderline elevations of one or more liver tests may occur in up to 15% of patients taking NSAIDs including indomethacin. These laboratory abnormalities may progress, may remain unchanged, or may be transient with continuing therapy. Notable elevations of ALT or AST (approximately three or more times the upper limit of normal) have been reported in approximately 1% of patients in clinical trials with NSAIDs. In addition, rare cases of severe hepatic reactions, including jaundice and fatal fulminant hepatitis, liver necrosis and hepatic failure, some of them with fatal outcomes have been reported.

A patient with symptoms and/or signs suggesting liver dysfunction, or in whom an abnormal liver test has occurred, should be evaluated for evidence of the development of a more severe hepatic reaction while on therapy with indomethacin. If clinical signs and symptoms consistent with liver disease develop, or if systemic manifestations occur (e.g., eosinophilia, rash, etc.), indomethacin should be discontinued.

Hematological Effects

Anemia is sometimes seen in patients receiving NSAIDs, including indomethacin. This may be due to fluid retention, occult or gross GI blood loss, or an incompletely described effect upon erythropoiesis. Patients on long-term treatment with NSAIDs, including indomethacin, should have their hemoglobin or hematocrit checked if they exhibit any signs or symptoms of anemia.

NSAIDs inhibit platelet aggregation and have been shown to prolong bleeding time in some patients. Unlike aspirin, their effect on platelet function is quantitatively less, of shorter duration, and reversible. Patients receiving indomethacin who may be adversely affected by alterations in platelet function, such as those with coagulation disorders or patients receiving anticoagulants, should be carefully monitored.

Preexisting Asthma

Patients with asthma may have aspirin-sensitive asthma. The use of aspirin in patients with aspirin-sensitive

asthma has been associated with severe bronchospasm which can be fatal. Since cross reactivity, including bronchospasm, between aspirin and other nonsteroidal anti-inflammatory drugs has been reported in such aspirin-sensitive patients, indomethacin should not be administered to patients with this form of aspirin sensitivity and should be used with caution in patients with preexisting asthma.

Information for Patients

Patients should be informed of the following information before initiating therapy with an NSAID and periodically during the course of ongoing therapy. Patients should also be encouraged to read the NSAID Medication Guide that accompanies each prescription dispensed.

1. Cardiovascular Thrombotic Events
  Advise patients to be alert for the symptoms of cardiovascular thrombotic events, including chest pain, shortness of breath, weakness, or slurring of speech, and to report any of these symptoms to their health care provider immediately [ see WARNINGS].
2. Indomethacin, like other NSAIDs, can cause GI discomfort and, rarely, serious GI side effects, such as ulcers and bleeding, which may result in hospitalization and even death. Although serious GI tract ulcerations and bleeding can occur without warning symptoms, patients should be alert for the signs and symptoms of ulcerations and bleeding, and should ask for medical advice when observing any indicative sign or symptoms including epigastric pain, dyspepsia, melena, and hematemesis. Patients should be apprised of the importance of this follow-up [see WARNINGS, Gastrointestinal Effects - Risk of Ulceration, Bleeding, and Perforation].
3. Serious Skin Reactions, including DRESS
  Advise patients to stop taking indomethacin capsules immediately if they develop any type of rash or fever and to contact their healthcare provider as soon as possible [see WARNINGS].
4. Heart Failure And Edema
  Advise patients to be alert for the symptoms of congestive heart failure including shortness of breath, unexplained weight gain, or edema and to contact their healthcare provider if such symptoms occur [see WARNINGS].
5. Patients should be informed of the warning signs and symptoms of hepatotoxicity (e.g., nausea, fatigue, lethargy, pruritus, jaundice, right upper quadrant tenderness, and “flu-like” symptoms). If these occur, patients should be instructed to stop therapy and seek immediate medical therapy.
6. Patients should be informed of the signs of an anaphylactic/anaphylactoid reaction (e.g. difficulty breathing, swelling of the face or throat). If these occur, patients should be instructed to seek immediate emergency help [see WARNINGS].
7. Fetal Toxicity
  Inform pregnant women to avoid use of indomethacin capsules and other NSAIDs starting at 30 weeks gestation because of the risk of the premature closing of the fetal ductus arteriosus. If treatment with indomethacin capsules is needed for a pregnant woman between about 20 to 30 weeks gestation, advise her that she may need to be monitored for oligohydramnios, if treatment continues for longer than 48 hours [see WARNINGS; Fetal Toxicity, PRECAUTIONS; Pregnancy].

Laboratory Tests

Because serious GI tract ulcerations and bleeding can occur without warning symptoms, physicians should monitor for signs or symptoms of GI bleeding. Patients on long-term treatment with NSAIDs should have their CBC and a chemistry profile checked periodically. If clinical signs and symptoms consistent with liver or renal disease develop, systemic manifestations occur (e.g., eosinophilia, rash, etc.) or if abnormal liver tests persist or worsen, indomethacin should be discontinued.

Drug Interactions

ACE-Inhibitors and Angiotensin II Antagonists

Reports suggest that NSAIDs may diminish the antihypertensive effect of ACE-inhibitors and angiotensin II antagonists. Indomethacin can reduce the antihypertensive effects of captopril and losartan. These interactions should be given consideration in patients taking NSAIDs concomitantly with ACE-inhibitors or angiotensin II antagonists. In some patients with compromised renal function, the co-administration of an NSAID and an ACE-inhibitor or an angiotensin II antagonist may result in further deterioration of renal function, including possible acute renal failure, which is usually reversible.

Aspirin

When indomethacin is administered with aspirin, its protein binding is reduced, although the clearance of free indomethacin is not altered. The clinical significance of this interaction is not known.

The use of indomethacin in conjunction with aspirin or other salicylates is not recommended. Controlled clinical studies have shown that the combined use of indomethacin and aspirin does not produce any greater therapeutic effect than the use of indomethacin alone. In a clinical study of the combined use of indomethacin and aspirin, the incidence of gastrointestinal side effects was significantly increased with combined therapy.

In a study in normal volunteers, it was found that chronic concurrent administration of 3.6 g of aspirin per day decreases indomethacin blood levels approximately 20%.

Indomethacin is not a substitute for low dose aspirin for cardiovascular protection.

Beta-adrenoceptor blocking agents

Blunting of the antihypertensive effect of beta-adrenoceptor blocking agents by non-steroidal anti-inflammatory drugs including indomethacin has been reported. Therefore, when using these blocking agents to treat hypertension, patients should be observed carefully in order to confirm that the desired therapeutic effect has been obtained.

Cyclosporine

Administration of non-steroidal anti-inflammatory drugs concomitantly with cyclosporine has been associated with an increase in cyclosporine-induced toxicity, possibly due to decreased synthesis of renal prostacyclin. NSAIDs should be used with caution in patients taking cyclosporine, and renal function should be carefully monitored.

Diflunisal

In normal volunteers receiving indomethacin, the administration of diflunisal decreased the renal clearance and significantly increased the plasma levels of indomethacin. In some patients, combined use of indomethacin and diflunisal has been associated with fatal gastrointestinal hemorrhage. Therefore, diflunisal and indomethacin should not be used concomitantly.

Digoxin

Indomethacin given concomitantly with digoxin has been reported to increase the serum concentration and prolong the half-life of digoxin. Therefore, when indomethacin and digoxin are used concomitantly, serum digoxin levels should be closely monitored.

Diuretics

In some patients, the administration of indomethacin can reduce the diuretic, natriuretic, and antihypertensive effects of loop, potassium-sparing, and thiazide diuretics. This response has been attributed to inhibition of renal prostaglandin synthesis.

Indomethacin reduces basal plasma renin activity (PRA), as well as those elevations of PRA induced by furosemide administration, or salt or volume depletion. These facts should be considered when evaluating plasma renin activity in hypertensive patients.

It has been reported that the addition of triamterene to a maintenance schedule of indomethacin resulted in reversible acute renal failure in two of four healthy volunteers. Indomethacin and triamterene should not be administered together.

Indomethacin and potassium-sparing diuretics each may be associated with increased serum potassium levels. The potential effects of indomethacin and potassium-sparing diuretics on potassium kinetics and renal function should be considered when these agents are administered concurrently.

Most of the above effects concerning diuretics have been attributed, at least in part, to mechanisms involving inhibition of prostaglandin synthesis by indomethacin.

During concomitant therapy with NSAIDs, the patient should be observed closely for signs of renal failure (see WARNINGS, Renal Effects), as well as to assure diuretic efficacy.

Lithium

Indomethacin capsules 50 mg t.i.d. produced a clinically relevant elevation of plasma lithium and reduction in renal lithium clearance in psychiatric patients and normal subjects with steady state plasma lithium concentrations. This effect has been attributed to inhibition of prostaglandin synthesis. As a consequence, when NSAIDs and lithium are given concomitantly, the patient should be carefully observed for signs of lithium toxicity. (Read circulars for lithium preparations before use of such concomitant therapy.) In addition, the frequency of monitoring serum lithium concentration should be increased at the outset of such combination drug treatment.

Methotrexate

NSAIDs have been reported to competitively inhibit methotrexate accumulation in rabbit kidney slices.

This may indicate that they could enhance the toxicity of methotrexate. Caution should be used when NSAIDs are administered concomitantly with methotrexate.

NSAIDs

The concomitant use of indomethacin with other NSAIDs is not recommended due to the increased possibility of gastrointestinal toxicity, with little or no increase in efficacy.

Oral anticoagulants

Clinical studies have shown that indomethacin does not influence the hypoprothrombinemia produced by anticoagulants. However, when any additional drug, including indomethacin, is added to the treatment of patients on anticoagulant therapy, the patients should be observed for alterations of the prothrombin time. In post-marketing experience, bleeding has been reported in patients on concomitant treatment with anticoagulants and indomethacin. Caution should be exercised when indomethacin and anticoagulants are administered concomitantly. The effects of warfarin and NSAIDs on GI bleeding are synergistic, such that users of both drugs together have a risk of serious GI bleeding higher than users of either drug alone.

Probenecid

When indomethacin is given to patients receiving probenecid, the plasma levels of indomethacin are likely to be increased. Therefore, a lower total daily dosage of indomethacin may produce a satisfactory therapeutic effect. When increases in the dose of indomethacin are made, they should be made carefully and in small increments.

Drug/Laboratory Test Interactions

False-negative results in the dexamethasone suppression test (DST) in patients being treated with indomethacin have been reported. Thus, results of the DST should be interpreted with caution in these patients.

Carcinogenesis, Mutagenesis, Impairment of Fertility

Carcinogenesis

In an 81-week chronic oral toxicity study in the rat at doses up to 1 mg/kg/day (0.05 times the maximum recommended human daily dose (MRHD) of 200 mg/day based on a mg/m^2 basis), indomethacin had no tumorigenic effect. Indomethacin produced no neoplastic or hyperplastic changes related to treatment in carcinogenic studies in the rat (dosing period 73 to 110 weeks) and the mouse (dosing period 62 to 88 weeks) at doses up to 1.5 mg/kg/day (0.04 times and 0.07 times the MRHD on a mg/m^2 basis, respectively) .

Mutagenesis

Indomethacin did not have any mutagenic effect in in vitro bacterial tests and a series of in vivo tests including the host-mediated assay, sex-linked recessive lethals in Drosophila, and the micronucleus test in mice.

Impairment of Fertility

Indomethacin at dosage levels up to 0.5 mg/kg/day had no effect on fertility in mice in a two generation reproduction study (0.01 times the MRHD on a mg/m^2 basis) or a two litter reproduction study in rats (0.02 times the MRHD on a mg/m^2 basis).

Pregnancy

Risk Summary

Use of NSAIDs, including indomethacin capsules, can cause premature closure of the fetal ductus arteriosus and fetal renal dysfunction leading to oligohydramnios and, in some cases, neonatal renal impairment. Because of these risks, limit dose and duration of indomethacin capsules use between about 20 and 30 weeks of gestation, and avoid indomethacin capsules use at about 30 weeks of gestation and later in pregnancy [ see WARNINGS; Fetal Toxicity].

Premature Closure of Fetal Ductus Arteriosus

Use of NSAIDs, including indomethacin capsules, at about 30 weeks gestation or later in pregnancy increases the risk of premature closure of the fetal ductus arteriosus.

Oligohydramnios/Neonatal Renal Impairment

Use of NSAIDs at about 20 weeks gestation or later in pregnancy has been associated with cases of fetal renal dysfunction leading to oligohydramnios, and in some cases, neonatal renal impairment.

Data from observational studies regarding other potential embryofetal risks of NSAID use in women in the first or second trimesters of pregnancy are inconclusive. In the general U.S. population, all clinically recognized pregnancies, regardless of drug exposure, have a background rate of 2-4% for major malformations, and 15-20% for pregnancy loss. In animal reproduction studies retarded fetal ossification was observed with administration of indomethacin to mice and rats during organogenesis at doses 0.1 and 0.2 times, respectively, the maximum recommended human dose (MRHD, 200 mg). In published studies in pregnant mice, indomethacin produced maternal toxicity and death, increased fetal resorptions, and fetal malformations at 0.1 times the MRHD. When rat and mice dams were dosed during the last three days of gestation, indomethacin produced neuronal necrosis in the offspring at 0.1 and 0.05 times the MRHD, respectively [see Data]. Based on animal data, prostaglandins have been shown to have an important role in endometrial vascular permeability, blastocyst implantation, and decidualization. In animal studies, administration of prostaglandin synthesis inhibitors such as indomethacin, resulted in increased pre- and post-implantation loss. Based on animal data, prostaglandins have been shown to have an important role in endometrial vascular permeability, blastocyst implantation, and decidualization. In animal studies, administration of prostaglandin synthesis inhibitors such as indomethacin, resulted in increased pre- and post-implantation loss. Prostaglandins also have been shown to have an important role in fetal kidney development. In published animal studies, prostaglandin synthesis inhibitors have been reported to impair kidney development when administered at clinically relevant doses.

Data

Animal Data

Reproductive studies were conducted in mice and rats at dosages of 0.5, 1.0, 2.0, and 4.0 mg/kg/day.

Except for retarded fetal ossification at 4 mg/kg/day considered secondary to the decreased average fetal weights, no increase in fetal malformations was observed as compared with control groups. Other studies in mice reported in the literature using higher doses (5 to 15 mg/kg/day) have described maternal toxicity and death, increased fetal resorptions, and fetal malformations.

In rats and mice, maternal indomethacin administration of 4.0 mg/kg/day (0.2 times and 0.1 times the MRHD on a mg/m^2 basis) during the last 3 days of gestation was associated with an increased incidence of neuronal necrosis in the diencephalon in the live-born fetuses, however, no increase in neuronal necrosis was observed at 2.0 mg/kg/day as compared to the control groups (0.1 times and 0.05 times the MRHD on a mg/m^2 basis). Administration of 0.5 or 4.0 mg/kg/day to offspring during the first 3 days of life did not cause an increase in neuronal necrosis at either dose level.

Clinical Considerations

Fetal/Neonatal Adverse Reactions

Premature Closure of Fetal Ductus Arteriosus:

Avoid use of NSAIDs in women at about 30 weeks gestation and later in pregnancy, because NSAIDs, including indomethacin capsules, can cause premature closure of the fetal ductus arteriosus (see WARNINGS; Fetal Toxicity) .

Oligohydramnios/Neonatal Renal Impairment

If an NSAID is necessary at about 20 weeks gestation or later in pregnancy, limit the use to the lowest effective dose and shortest duration possible. If indomethacin capsules treatment extends beyond 48 hours, consider monitoring with ultrasound for oligohydramnios. If oligohydramnios occurs, discontinue indomethacin capsules and follow up according to clinical practice (see WARNINGS; Fetal Toxicity).

Data

Human Data

Premature Closure of Fetal Ductus Arteriosus:

Published literature reports that the use of NSAIDs at about 30 weeks of gestation and later in pregnancy may cause premature closure of the fetal ductus arteriosus.

Oligohydramnios/Neonatal Renal Impairment:

Published studies and postmarketing reports describe maternal NSAID use at about 20 weeks gestation or later in pregnancy associated with fetal renal dysfunction leading to oligohydramnios, and in some cases, neonatal renal impairment. These adverse outcomes are seen, on average, after days to weeks of treatment, although oligohydramnios has been infrequently reported as soon as 48 hours after NSAID initiation. In many cases, but not all, the decrease in amniotic fluid was transient and reversible with cessation of the drug. There have been a limited number of case reports of maternal NSAID use and neonatal renal dysfunction without oligohydramnios, some of which were irreversible. Some cases of neonatal renal dysfunction required treatment with invasive procedures, such as exchange transfusion or dialysis.

Methodological limitations of these postmarketing studies and reports include lack of a control group; limited information regarding dose, duration, and timing of drug exposure; and concomitant use of other medications. These limitations preclude establishing a reliable estimate of the risk of adverse fetal and neonatal outcomes with maternal NSAID use. Because the published safety data on neonatal outcomes involved mostly preterm infants, the generalizability of certain reported risks to the full-term infant exposed to NSAIDs through maternal use is uncertain.

Labor and Delivery

There are no studies on the effects of indomethacin capsules during labor and delivery. In animal studies, NSAIDs, including indomethacin, inhibit prostaglandin synthesis, caused delayed parturition, and increase the incidence of stillbirths.

Use in Nursing Mothers

Indomethacin is excreted in the milk of lactating mothers. The development and health benefits of breastfeeding should be considered along with the mother’s clinical need for indomethacin capsules and any potential adverse effects on the breastfed infant from the indomethacin capsules or from the underlying maternal condition.

Pediatric Use

Safety and effectiveness in pediatric patients 14 years of age and younger has not been established. Indomethacin should not be prescribed for pediatric patients 14 years of age and younger unless toxicity or lack of efficacy associated with other drugs warrants the risk.

In experience with more than 900 pediatric patients reported in the literature or to the manufacturer who were treated with indomethacin capsules, side effects in pediatric patients were comparable to those reported in adults. Experience in pediatric patients has been confined to the use of indomethacin capsules.

If a decision is made to use indomethacin for pediatric patients two years of age or older, such patients should be monitored closely and periodic assessment of liver function is recommended. There have been cases of hepatotoxicity reported in pediatric patients with juvenile rheumatoid arthritis, including fatalities. If indomethacin treatment is instituted, a suggested starting dose is 1-2 mg/kg/day given in divided doses. Maximum daily dosage should not exceed 3 mg/kg/day or 150-200 mg/day, whichever is less. Limited data are available to support the use of a maximum daily dosage of 4 mg/kg/day or 150-200 mg/day, whichever is less. As symptoms subside, the total daily dosage should be reduced to the lowest level required to control symptoms, or the drug should be discontinued.

Geriatric Use

As with any NSAID, caution should be exercised in treating the elderly (65 years and older) since advancing age appears to increase the possibility of adverse reactions [see WARNINGS, Gastrointestinal Effects - Risk of Ulceration, Bleeding, and Perforation and DOSAGE AND ADMINISTRATION]. Elderly patients seem to tolerate ulceration or bleeding less well than other individuals and many spontaneous reports of fatal GI events are in this population [see WARNINGS, Gastrointestinal Effects - Risk of Ulceration, Bleeding, and Perforation].

Indomethacin may cause confusion or, rarely, psychosis [see ADVERSE REACTIONS]; physicians should remain alert to the possibility of such adverse effects in the elderly.

This drug is known to be substantially excreted by the kidney and the risk of toxic reactions to this drug may be greater in patients with impaired renal function. Because elderly patients are more likely to have decreased renal function, care should be taken in dose selection and it may be useful to monitor renal function [see WARNINGS, Renal Effects].

ADVERSE REACTIONS

The adverse reactions for indomethacin capsules listed in the following table have been arranged into two groups: (1) incidence greater than 1%; and (2) incidence less than 1%. The incidence for group (1) was obtained from 33 double-blind controlled clinical trials reported in the literature (1,092 patients). The incidence for group (2) was based on reports in clinical trials, in the literature, and on voluntary reports since marketing. The probability of a causal relationship exists between indomethacin and these adverse reactions, some of which have been reported only rarely.

Incidence greater than 1% | Incidence less than 1%
GASTROINTESTINAL
nausea * with or without vomiting; dyspepsia * (including indigestion, heartburn and epigastric pain); diarrhea; abdominal distress or pain; constipation | anorexia; bloating (includes distension); flatulence; peptic ulcer; gastroenteritis; rectal bleeding; proctitis; single or multiple ulcerations, including perforation and hemorrhage of the esophagus, stomach, duodenum or small and large intestines; intestinal ulceration associated with stenosis and obstruction | gastrointestinal bleeding without obvious ulcer formation and perforation of pre-existing sigmoid lesions (diverticulum, carcinoma, etc.) development of ulcerative colitis and regional ileitis; ulcerative stomatitis; toxic hepatitis and jaundice (some fatal cases have been reported); intestinal strictures (diaphragms)
CENTRAL NERVOUS SYSTEM
headache (11.7%); dizziness *; vertigo; somnolence; depression and fatigue (including malaise and listlessness) | anxiety (includes nervousness); muscle weakness; involuntary muscle movements; insomnia; muzziness; psychic disturbances including psychotic episodes; mental confusion; drowsiness | light-headedness; syncope; paresthesia; aggravation of epilepsy and parkinsonism; depersonalization; coma; peripheral neuropathy; convulsion; dysarthria
SPECIAL SENSES
tinnitus | ocular- corneal deposits and retinal disturbances, including those of the macula, have been reported in some patients on prolonged therapy with indomethacin | blurred vision; diplopia; hearing disturbances, deafness
CARDIOVASCULAR
None | hypertension; hypotension; tachycardia; chest pain | congestive heart failure; arrhythmia; palpitations
METABOLIC
None | edema; weight gain; fluid retention; flushing or sweating | hyperglycemia; glycosuria; hyperkalemia
INTEGUMENTARY
None | pruritus; rash; urticaria; petechiae or ecchymosis | exfoliative dermatitis; erythema nodosum; loss of hair; Stevens-Johnson Syndrome; erythema multiforme; toxic epidermal necrolysis
HEMATOLOGIC
None | leukopenia; bone marrow depression; anemia secondary to obvious or occult gastrointestinal bleeding | aplastic anemia; hemolytic anemia; agranulocytosis; thrombocytopenic purpura; disseminated intravascular coagulation
HYPERSENSITIVITY
None | acute anaphylaxis; acute respiratory distress; rapid fall in blood pressure resembling a shock-like state; angioedema | dyspnea; asthma; purpura; angiitis; pulmonary edema; fever
GENITOURINARY
None | hematuria; vaginal bleeding; proteinuria; nephrotic syndrome; interstitial nephritis | BUN elevation; renal insufficiency, including renal failure
MISCELLANEOUS
None | epistaxis; breast changes, including enlargement and tenderness, or gynecomastia

* Reactions occurring in 3% to 9% of patients treated with indomethacin capsules. (Those reactions occurring in less than 3% of the patients are unmarked.)

Causal relationship unknown: Other reactions have been reported but occurred under circumstances where a causal relationship could not be established. However, in these rarely reported events, the possibility cannot be excluded. Therefore, these observations are being listed to serve as alerting information to physicians:

Cardiovascular: Thrombophlebitis

Hematologic: Although there have been several reports of leukemia, the supporting information is weak

Genitourinary: Urinary frequency.

A rare occurrence of fulminant necrotizing fasciitis, particularly in association with Group A β hemolytic streptococcus, has been described in persons treated with non-steroidal anti-inflammatory agents, including indomethacin, sometimes with fatal outcome [see also PRECAUTIONS, General].

OVERDOSAGE

The following symptoms may be observed following overdosage: nausea, vomiting, intense headache, dizziness, mental confusion, disorientation, or lethargy. There have been reports of paresthesias, numbness, and convulsions.

Treatment is symptomatic and supportive. The stomach should be emptied as quickly as possible if the ingestion is recent. If vomiting has not occurred spontaneously, the patient should be induced to vomit with syrup of ipecac. If the patient is unable to vomit, gastric lavage should be performed. Once the stomach has been emptied, 25 or 50 g of activated charcoal may be given. Depending on the condition of the patient, close medical observation and nursing care may be required. The patient should be followed for several days because gastrointestinal ulceration and hemorrhage have been reported as adverse reactions of indomethacin. Use of antacids may be helpful.

The oral LD50 of indomethacin in mice and rats (based on 14 day mortality response) was 50 and 12 mg/kg, respectively.

DOSAGE AND ADMINISTRATION

Carefully consider the potential benefits and risks of indomethacin and other treatment options before deciding to use indomethacin . Use the lowest effective dose for the shortest duration consistent with individual patient treatment goals [see WARNINGS].

After observing the response to initial therapy with indomethacin, the dose and frequency should be adjusted to suit an individual patient’s needs.

Indomethacin is available as 25 mg capsules

Adverse reactions appear to correlate with the size of the dose of indomethacin in most patients but not all. Therefore, every effort should be made to determine the smallest effective dosage for the individual patient.

Pediatric Use

Indomethacin ordinarily should not be prescribed for pediatric patients 14 years of age and under (see PRECAUTIONS, Pediatric Use).

Adult Use

Dosage Recommendations for Active Stages of the Following:

1. Moderate to severe rheumatoid arthritis including acute flares of chronic disease; moderate to severe ankylosing spondylitis; and moderate to severe osteoarthritis.
  Suggested Dosage:
  Indomethacin capsules 25 mg b.i.d. or t.i.d. If this is well tolerated, increase the daily dosage by 25 or by 50 mg, if required by continuing symptoms, at weekly intervals until a satisfactory response is obtained or until a total daily dose of 150-200 mg is reached. DOSES ABOVE THIS AMOUNT GENERALLY DO NOT INCREASE THE EFFECTIVENESS OF THE DRUG.

In patients who have persistent night pain and/or morning stiffness, the giving of a large portion, up to a maximum of 100 mg, of the total daily dose at bedtime may be helpful in affording relief. The total daily dose should not exceed 200 mg. In acute flares of chronic rheumatoid arthritis, it may be necessary to increase the dosage by 25 mg or, if required, by 50 mg daily.

If minor adverse effects develop as the dosage is increased, reduce the dosage rapidly to a tolerated dose and OBSERVE THE PATIENT CLOSELY.

If severe adverse reactions occur, STOP THE DRUG. After the acute phase of the disease is under control, an attempt to reduce the daily dose should be made repeatedly until the patient is receiving the smallest effective dose or the drug is discontinued.

Careful instructions to, and observations of, the individual patient are essential to the prevention of serious, irreversible, including fatal, adverse reactions.

As advancing years appear to increase the possibility of adverse reactions, indomethacin should be used with greater care in the elderly [see PRECAUTIONS, Geriatric Use].

2. Acute painful shoulder (bursitis and/or tendinitis).

Initial Dose:

75-150 mg daily in 3 or 4 divided doses.

The drug should be discontinued after the signs and symptoms of inflammation have been controlled for several days. The usual course of therapy is 7-14 days.

3. Acute gouty arthritis.

Suggested Dosage:

Indomethacin capsules 50 mg t.i.d. until pain is tolerable. The dose should then be rapidly reduced to complete cessation of the drug. Definite relief of pain has been reported within 2 to 4 hours.

Tenderness and heat usually subside in 24 to 36 hours, and swelling gradually disappears in 3 to 5 days.

HOW SUPPLIED

Indomethacin Capsules, USP are available containing 25 mg of indomethacin.

The 25 mg (green/green) capsules are imprinted “CE” in black ink on cap and imprinted “57” in black ink on body, filled with white powder and are supplied in bottles of 90 (NDC 62135-067-90), 180 (NDC 62135-067-18) Capsules.

Store at 20˚ to 25˚C (68˚ to 77˚F) [see USP controlled room temperature].

Manufactured for:
Chartwell RX, LLC.
Congers, NY 10920
L71083
Rev. 09/2022

Medication Guide for Nonsteroidal Anti-inflammatory Drugs (NSAIDs)

What is the most important information I should know about medicines called Nonsteroidal Anti- inflammatory Drugs (NSAIDs)?

NSAIDs can cause serious side effects, including:

- Increased risk of a heart attack or stroke that can lead to death. This risk may happen early in treatment and may increase:
  - with increasing doses of NSAIDs
  - with longer use of NSAIDs

Do not take NSAIDs right before or after a heart surgery called a “coronary artery bypass graft (CABG)."

Avoid taking NSAIDs after a recent heart attack, unless your healthcare provider tells you to. You may have an increased risk of another heart attack if you take NSAIDs after a recent heart attack.

- Increased risk of bleeding, ulcers, and tears (perforation) of the esophagus (tube leading from the mouth to the stomach), stomach and intestines:
  - anytime during use
  - without warning symptoms
  - that may cause death

The risk of getting an ulcer or bleeding increases with:

- past history of stomach ulcers, or stomach or intestinal bleeding with use of NSAIDs
- taking medicines called “corticosteroids”, “anticoagulants”, “SSRIs”, or “SNRIs”
- increasing doses of NSAIDs o older age
- longer use of NSAIDs o poor health
- smoking o advanced liver disease
- drinking alcohol o bleeding problems

NSAIDs should only be used:

- exactly as prescribed
- at the lowest dose possible for your treatment
- for the shortest time needed

What are NSAIDs?

NSAIDs are used to treat pain and redness, swelling, and heat (inflammation) from medical conditions such as different types of arthritis, menstrual cramps, and other types of short-term pain.

Who should not take NSAIDs?

Do not take NSAIDs:

- if you have had an asthma attack, hives, or other allergic reaction with aspirin or any other NSAIDs.
- right before or after heart bypass surgery.

Before taking NSAIDS, tell your healthcare provider about all of your medical conditions, including if you:

- have liver or kidney problems
- have high blood pressure
- have asthma
- are pregnant or plan to become pregnant. Taking NSAIDs at about 20 weeks of pregnancy or later may harm your unborn baby. If you need to take NSAIDs for more than 2 days when you are between 20 and 30 weeks of pregnancy, your healthcare provider may need to monitor the amount of fluid in your womb around your baby. You should not take NSAIDs after 29 weeks of pregnancy.
- are breastfeeding or plan to breast feed.

Tell your healthcare provider about all of the medicines you take, including prescription or over-the-counter medicines, vitamins or herbal supplements. NSAIDs and some other medicines can interact with each other and cause serious side effects. Do not start taking any new medicine without talking to your healthcare provider first.

What are the possible side effects of NSAIDs?

NSAIDs can cause serious side effects, including:

See “What is the most important information I should know about medicines called Nonsteroidal Anti-inflammatory Drugs (NSAIDs)?

- new or worse high blood pressure
- heart failure
- liver problems including liver failure
- kidney problems including kidney failure
- low red blood cells (anemia)
- life-threatening skin reactions
- life-threatening allergic reactions
- Other side effects of NSAIDs include: stomach pain, constipation, diarrhea, gas, heartburn, nausea, vomiting, and dizziness.

Get emergency help right away if you get any of the following symptoms:

- shortness of breath or trouble breathing • slurred speech
- chest pain • swelling of the face or throat
- weakness in one part or side of your body

Stop taking your NSAID and call your healthcare provider right away if you get any of the following symptoms:

- nausea • vomit blood
- more tired or weaker than usual • there is blood in your bowel movement or it is black and sticky like tar
- diarrhea • unusual weight gain
- itching • skin rash or blisters with fever
- your skin or eyes look yellow • swelling of the arms, legs, hands and feet
- indigestion or stomach pain
- flu-like symptoms

If you take too much of your NSAID, call your healthcare provider or get medical help right away. These are not all the possible side effects of NSAIDs. For more information, ask your healthcare provider or pharmacist about NSAIDs.

Call your doctor for medical advice about side effects. You may report side effects to FDA at 1-800-FDA-1088.

Other information about NSAIDs

- Aspirin is an NSAID but it does not increase the chance of a heart attack. Aspirin can cause bleeding in the brain, stomach, and intestines. Aspirin can also cause ulcers in the stomach and intestines.
- Some NSAIDs are sold in lower doses without a prescription (over-the counter). Talk to your healthcare provider before using over-the-counter NSAIDs for more than 10 days.

General information about the safe and effective use of NSAIDs

Medicines are sometimes prescribed for purposes other than those listed in a Medication Guide. Do not use NSAIDs for a condition for which it was not prescribed. Do not give NSAIDs to other people, even if they have the same symptoms that you have. It may harm them.

If you would like more information about NSAIDs, talk with your healthcare provider. You can ask your pharmacist or healthcare provider for information about NSAIDs that is written for health professionals.

Manufactured for: Chartwell RX, LLC, Congers, NY 10920

For more information, contact Chartwell RX, LLC at 845-232-1683.

This Medication Guide has been approved by the U.S. Food and Drug Administration. Revised: 09/2022

L71084

PACKAGE LABEL-PRINCIPAL DISPLAY PANEL

Indomethacin Capsules, USP 25 mg - NDC 62135-067-90 - 90 Capsules Label

Indomethacin Capsules, USP 25 mg - NDC 62135-067-18 - 180 Capsules Label